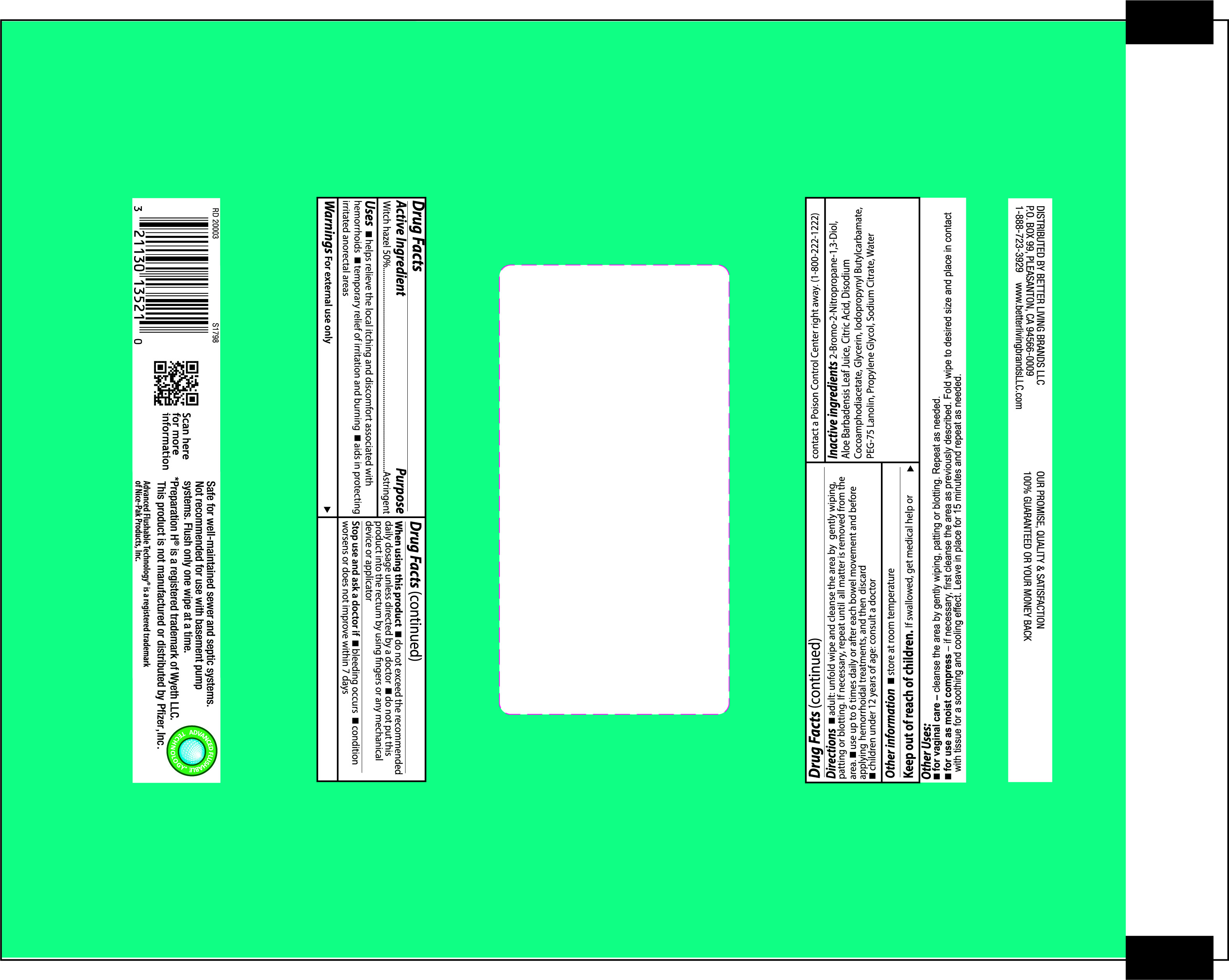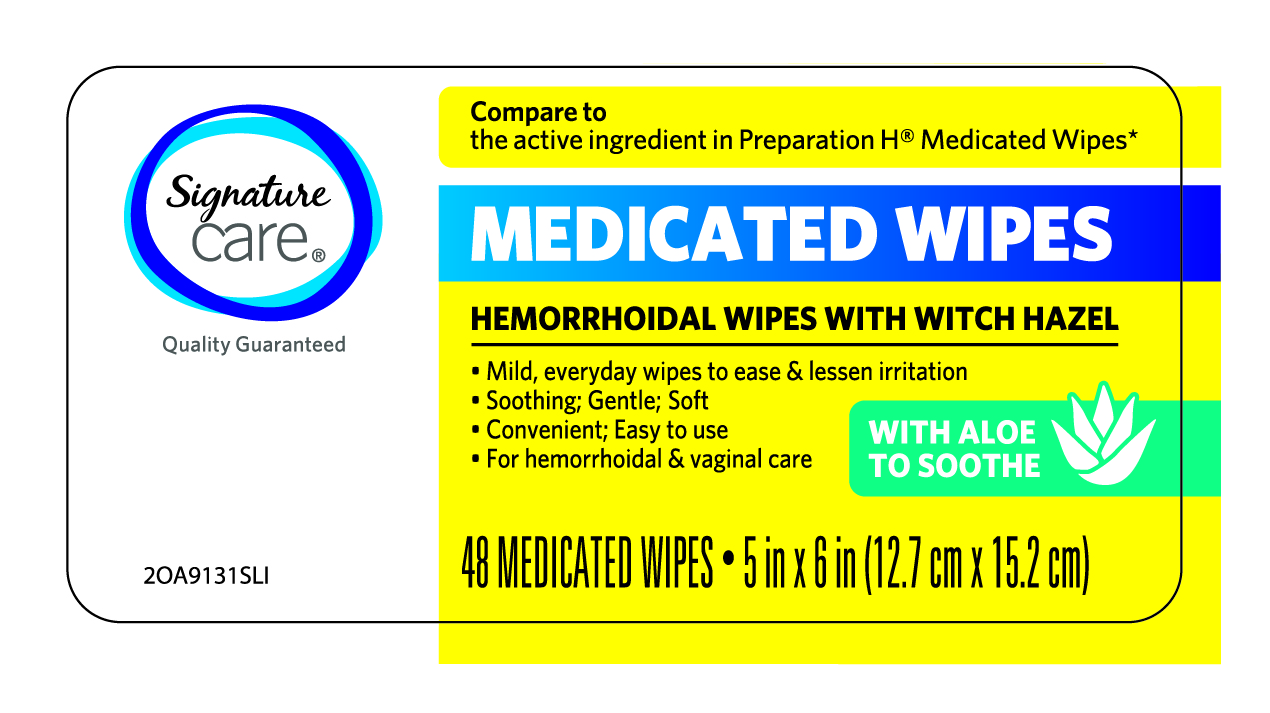 DRUG LABEL: Signature Care Medicated Wipes Hemorrhoidal Wipes with Witch Hazel
NDC: 21130-800 | Form: CLOTH
Manufacturer: Better Living Brands LLC
Category: otc | Type: HUMAN OTC DRUG LABEL
Date: 20241107

ACTIVE INGREDIENTS: WITCH HAZEL 0.5 mg/1 mL
INACTIVE INGREDIENTS: PROPYLENE GLYCOL; SODIUM CITRATE; IODOPROPYNYL BUTYLCARBAMATE; BRONOPOL; ALOE VERA LEAF; CITRIC ACID MONOHYDRATE; WATER; PEG-75 LANOLIN; DISODIUM COCOAMPHODIACETATE; GLYCERIN

Signature Care Medicated Wipes Hemorrhoidal Wipes with Witch Hazel

ACTIVE INGREDIENT

Witch hazel 50%

PURPOSE

Astringent

USES

helps relieve the local itching and discomfort associated with hemorrhoids

temporary relief of irritation and burning

aids in protecting irritated anorectal areas

WARNINGS

For external use only

WHEN USING THIS PRODUCT

do not exceed the recommended daily dosage unless directed by a doctor

do not put this product into the rectum by using fingers or any mechanical device or applicator

STOP USE AND ASK A DOCTOR IF

bleeding occurs

condition worsens or does not improve within 7 days

DIRECTIONS

adult: unfold wipe and cleanse the area by gently wiping, patting or blotting. If necessary, repeat until all matter is removed from the area

use up to 6 times daily or after each bowel movement and before applying topical hemorrhoidal treatments, and then discard

children under 12 years of age: consult a doctor

OTHER INFORMATION

store at room temperature

INACTIVE INGREDIENTS

2-Bromo-2-Nitropropane-1,3-Diol, Aloe Barbadensis Leaf Juice, Citric Acid, Disodium Cocoamphodiacetate, Glycerin, Iodopropynyl Butylcarbamate, PEG-75 Lanolin, Propylene Glycol, Sodium Citrate, Water

Other Uses

for vaginal care - cleanse the area by gently wiping, patting or blotting. Repeat as needed.

for use as a moist compress - if necessary, first cleanse the area as previously described. Fold wipe to desired size and place in contact with tissue for a soothing and cooling effect. Leave in place for up to 15 minutes and repeat as needed.

FOR COMMENTS OR QUESTIONS PLEASE

DISTRIBUTED BY BETTER LIVING BRANDS LLC

P.O. BOX 99, PLEASANTON, CA 94566-0009

Keep out of reach of children

If swallowed, get medical help or contact a Poison Control Center right away.

PRINCIPAL DISPLAY PANEL - LID LABEL

Signature Care

Quality Guaranteed

Compare to the active ingredient in Preparation H(R) Medicated Wipes*

MEDICATED WIPES

HEMORRHOIDAL WIPES WITH WITCH HAZEL

Mild, everyday wipes to ease & lessen irritation

Soothing; Gentle; Soft

Convenient; Easy to use

For hemorrhoidal & vaginal care

WITH ALOE TO SOOTHE

48 MEDICATED WIPES

5 in X 6 in (12.7 cm x 15.2 cm)

2OA9131SLI